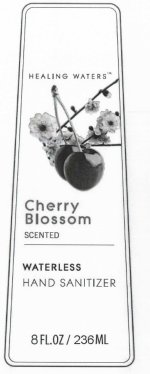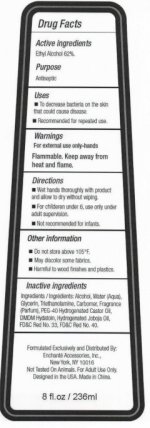 DRUG LABEL: Healing Waters Cherry Blossom Scented Waterless Hand Sanitizer
NDC: 50563-152 | Form: GEL
Manufacturer: Enchante Accessories, Inc
Category: otc | Type: HUMAN OTC DRUG LABEL
Date: 20100602

ACTIVE INGREDIENTS: ALCOHOL 62 mL/100 mL
INACTIVE INGREDIENTS: ALCOHOL; WATER; GLYCERIN; TROLAMINE; CARBOMER 934; POLYOXYL 40 HYDROGENATED CASTOR OIL; D&C RED NO. 33; FD&C RED NO. 40; JOJOBA OIL

Healing Waters Cherry Blossom Scented Waterless Hand Sanitizer

Active Ingredients

Ethyl Alcohol 62 percent

Purpose

Antiseptic

Uses

To decrease bacteria on the skin that could cause disease.

Recommended for repeated use.

Warnings

For external use only-hands

Flammable, Keep away from heat and flame.

Directions

Wet hands thoroughly with product and allow to dry without wiping.

For children under 6, use only under adult supervision.

Not recommended for infants.

Other Information

Do not store above 105 fahrenheit.

May discolor some fabrics.

Harmful to wood finishes and plastics.

Inactive Ingredients

Ingredients: Alcohol, Water (Aqua), Triethanolamine, Carbomer, Fragrance (Parfum), PEG 40 Hydrogenated Castor Oil,

DMDM Hydatoin, Hydrogenated Joboja Oil, FD and C Red No. 33, FD and C Red No. 40.

DESCRIPTION

Formulated Exclusively and Distributed By:
Enchante Accessories, Inc.,
New York, NY 10016
Not Tested On Animals. For Adult Use Only.
Designed in the USA. Made in China.

PACKAGE LABEL

Healing Waters

Cherry Blossom

Scented

Waterless

Hand Sanitizer

8 FL. OZ 236 ML